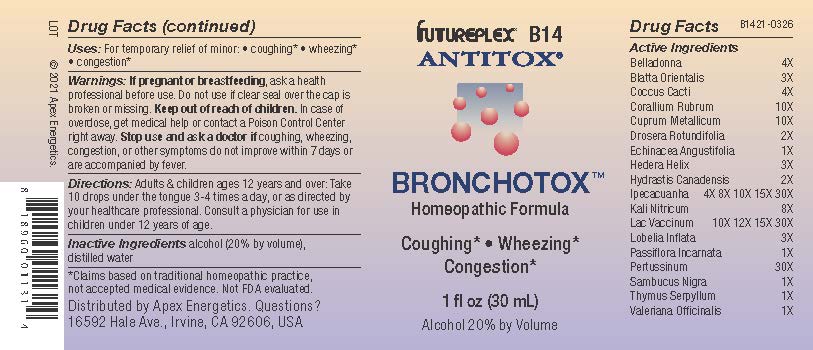 DRUG LABEL: B14
NDC: 63479-0214 | Form: SOLUTION/ DROPS
Manufacturer: Apex Energetics Inc.
Category: homeopathic | Type: HUMAN OTC DRUG LABEL
Date: 20240108

ACTIVE INGREDIENTS: ECHINACEA ANGUSTIFOLIA 1 [hp_X]/1 mL; COW MILK 30 [hp_X]/1 mL; LOBELIA INFLATA 3 [hp_X]/1 mL; PASSIFLORA INCARNATA FLOWERING TOP 1 [hp_X]/1 mL; HUMAN SPUTUM, BORDETELLA PERTUSSIS INFECTED 30 [hp_X]/1 mL; THYMUS SERPYLLUM 1 [hp_X]/1 mL; VALERIAN 1 [hp_X]/1 mL; ATROPA BELLADONNA 4 [hp_X]/1 mL; SAMBUCUS NIGRA FLOWERING TOP 1 [hp_X]/1 mL; PROTORTONIA CACTI 4 [hp_X]/1 mL; HEDERA HELIX FLOWERING TWIG 3 [hp_X]/1 mL; IPECAC 30 [hp_X]/1 mL; POTASSIUM NITRATE 8 [hp_X]/1 mL; CORALLIUM RUBRUM EXOSKELETON 10 [hp_X]/1 mL; COPPER 10 [hp_X]/1 mL; DROSERA ROTUNDIFOLIA 2 [hp_X]/1 mL; GOLDENSEAL 2 [hp_X]/1 mL; BLATTA ORIENTALIS 3 [hp_X]/1 mL
INACTIVE INGREDIENTS: ALCOHOL; WATER

B14

Active Ingredients
Belladonna | 4X
Blatta Orientalis | 3X
Coccus Cacti | 4X
Corallium Rubrum | 10X
Cuprum Metallicum | 10X
Drosera Rotundifolia | 2X
Echinacea Angustifolia | 1X
Hedera Helix | 3X
Hydrastis Canadensis | 2X
Ipecacuanha | 4X 8X 10X 15X 30X
Kali Nitricum | 8X
Lac Vaccinum | 10X 12X 15X 30X
Lobelia Inflata | 3X
Passiflora Incarnata | 1X
Pertussinum | 30X
Sambucus Nigra | 1X
Thymus Serpyllum | 1X
Valeriana Officinalis | 1X

INDICATIONS AND USAGE

Uses:

For temporary relief of minor:

coughing*

wheezing*

congestion*

*Claims based on traditional homeopathic practice, not accepted medical evidence. Not FDA evaluated.

Warnings:

PREGNANCY OR BREAST FEEDING

If pregnant or breastfeeding, ask a health professional before use.

Do not use if clear seal over the cap is broken or missing.

Keep out of reach of children. In case of overdose, get medical help or contact a Poison Control Center right away.

Stop use and ask a doctor if coughing, wheezing, congestion, or other symptoms do not improve within 7 days or are accompanied by fever.

Directions:

Adults & children ages 12 years and over: Take 10 drops under the tongue 3-4 times a day, or as directed by your healthcare professional. Consult a physician for use in children under 12 years of age.

Inactive Ingredients

alcohol (20% by volume), distilled water

Distributed by Apex Energetics. Questions?

16592 Hale Ave., Irvine, CA 92606, USA

PACKAGE LABEL

FUTUREPLEX® B14

ANTITOX®

BRONCHOTOX™

Homeopathic Formula

Coughing*

Wheezing*

Congestion*

1 fl oz (30 mL)

Alcohol 20% by Volume